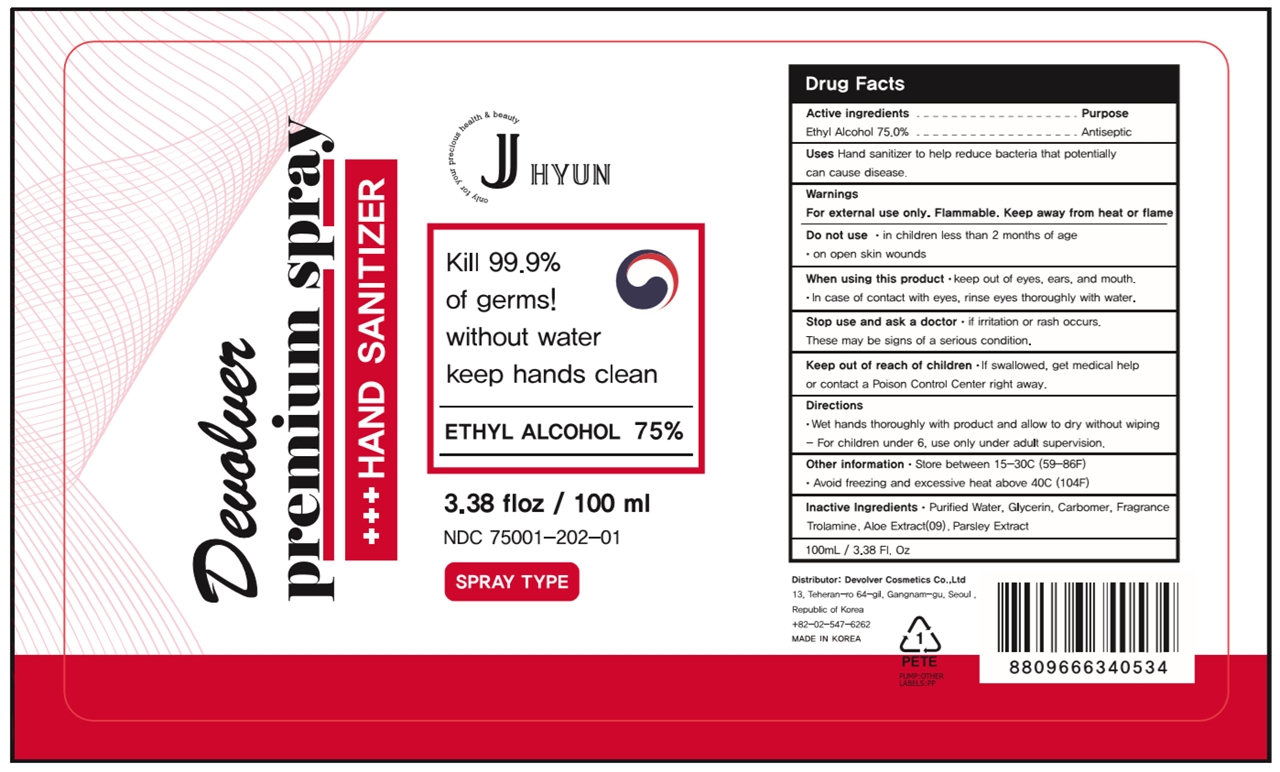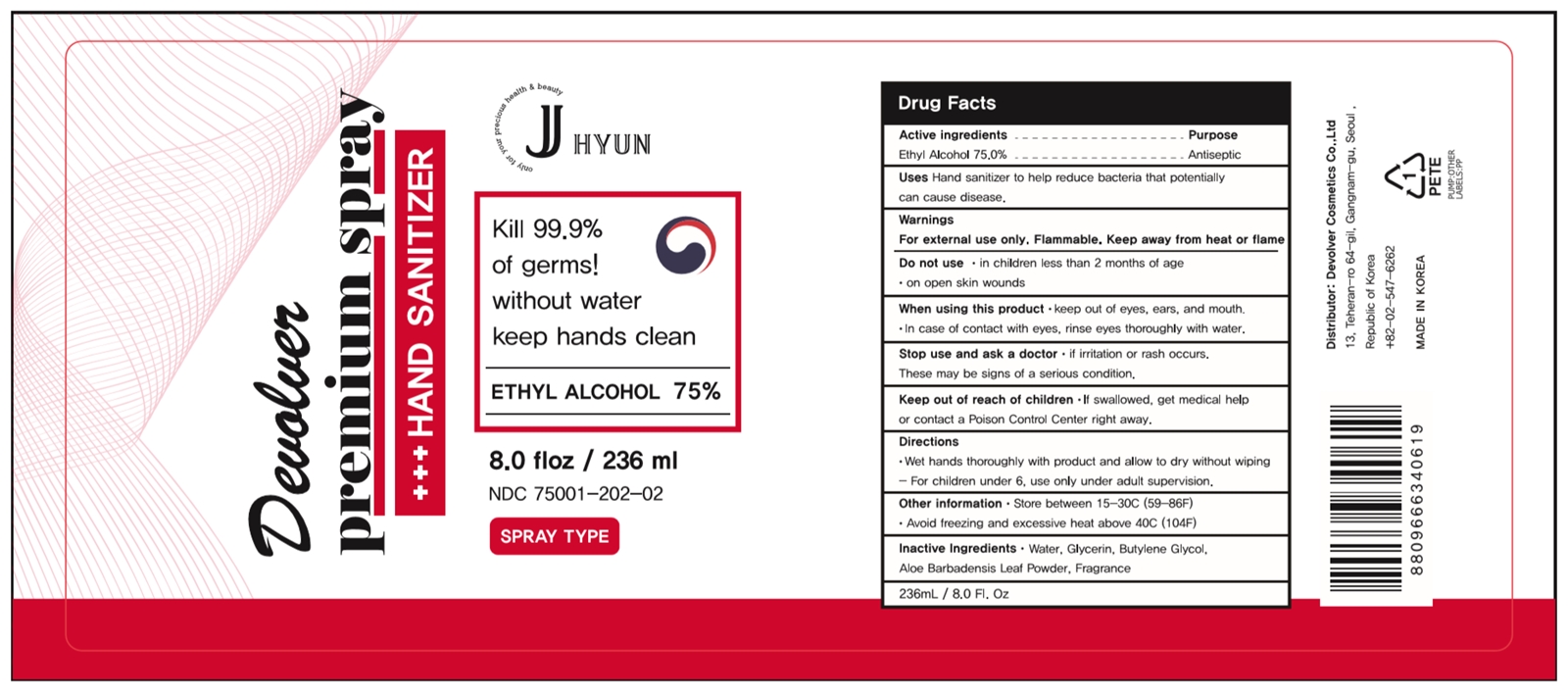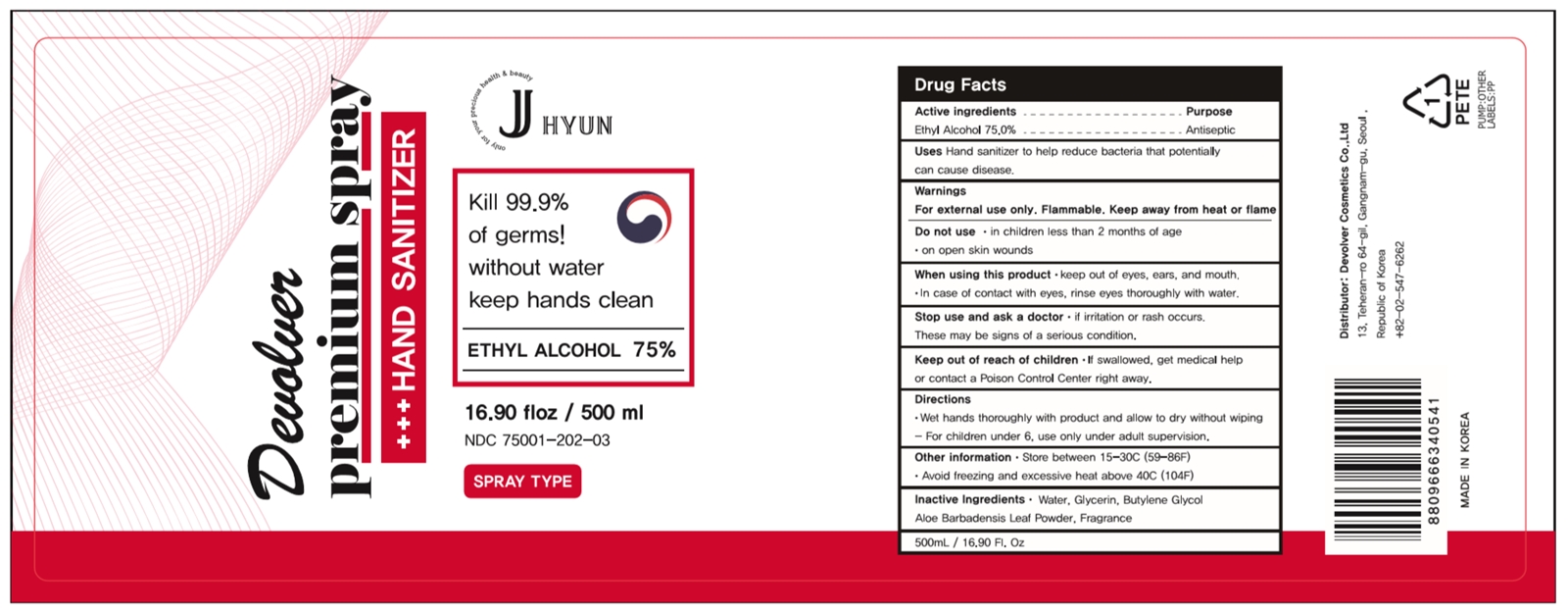 DRUG LABEL: Devolver Premium-Spray
NDC: 75001-202 | Form: LIQUID
Manufacturer: Devolver Cosmetics Co., Ltd
Category: otc | Type: HUMAN OTC DRUG LABEL
Date: 20200602

ACTIVE INGREDIENTS: ALCOHOL 75.0006 mL/100 mL
INACTIVE INGREDIENTS: FRAGRANCE LAVENDER & CHIA F-153480; WATER; BUTYLENE GLYCOL; ALOE VERA LEAF; GLYCERIN

75001-202

Active ingredient

Ethyl Alcohol 75%

Purpose

Antiseptic

Use

Hand sanitizer to help reduce bacteria that potentially can cause disease.

Warnings

For external use only. Flammable. Keep away from heat or flame.

Do not use

in children less than 2 months of age

on open skin wounds

When using this product

keep out of eyes, ears, and mouth.

In case of contact with eyes, rinse eyes thoroughly with water.

Stop use and ask a doctor

if irritation or rash occurs.

These may be signs of a serious condition.

Keep out of reach of children.

If swallowed, get medical help or contact a Poison Control Center right away.

Directions

Wet hands thoroughly with product and allow to dry without wiping.

For children under 6, use only under adult supervision.

Other information

Store between 15-30C (59-86F)

Avoid freezing and excessive heat above 40C (104F)

Inactive ingredients

Water, Glycerin, Butylene Glyol, Aloe Barbadensis Leaf Powder, Fragrance